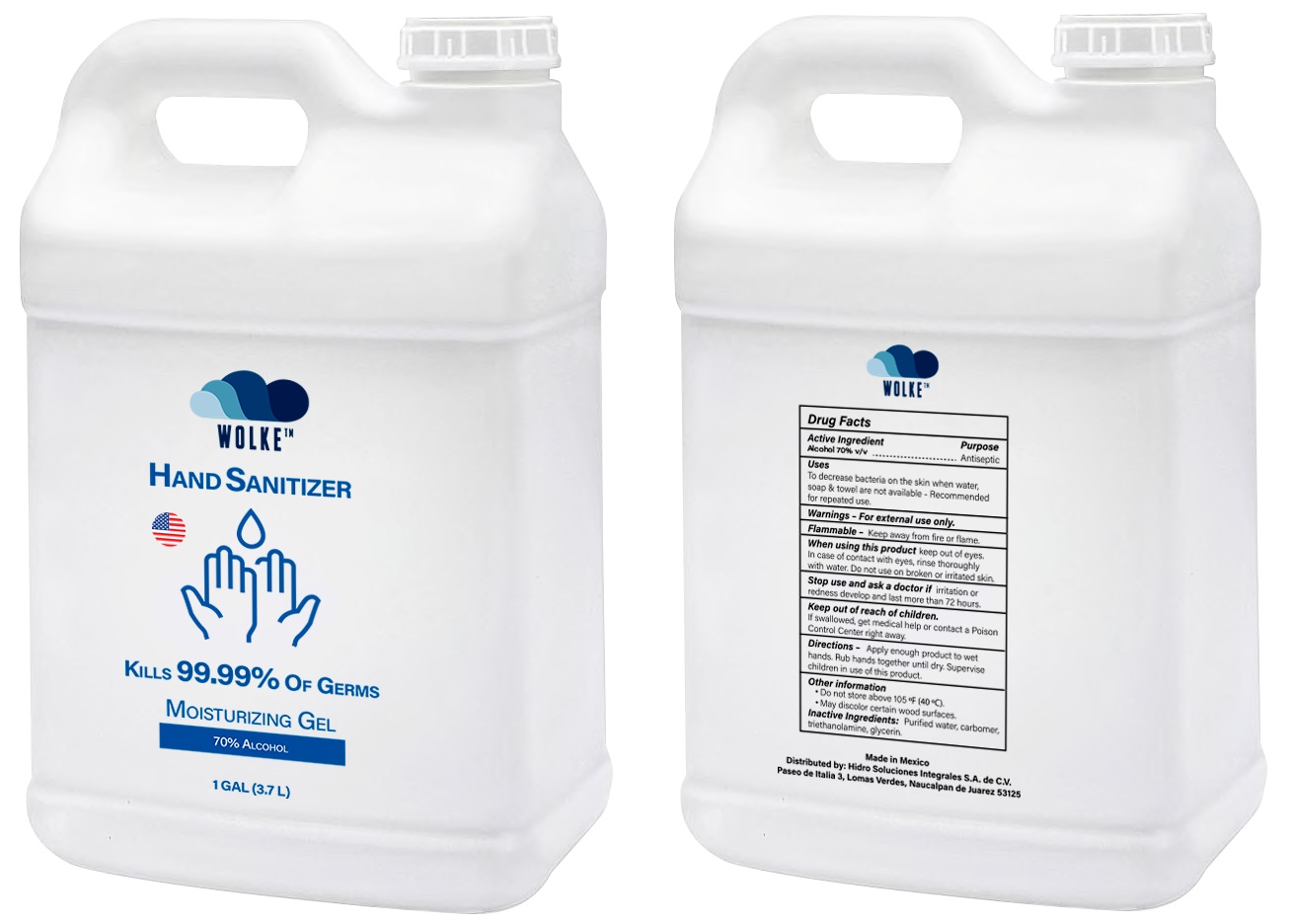 DRUG LABEL: HAND SANITIZER WOLKE
NDC: 78207-001 | Form: GEL
Manufacturer: Hidro Soluciones Integrales, S.A. de C.V.
Category: otc | Type: HUMAN OTC DRUG LABEL
Date: 20200817

ACTIVE INGREDIENTS: ALCOHOL 0.7 mL/1 mL
INACTIVE INGREDIENTS: WATER; CARBOMER HOMOPOLYMER, UNSPECIFIED TYPE; TROLAMINE; GLYCERIN

HAND SANITIZER WOLKE

Active Ingredient

Alcohol 70% v/v

Purpose

Antiseptic

Uses

To decrease bacteria on the skin when water, soap & towel are not available - Recommended for repeated use.

Warnings

- For external use only.

Flammable - Keep away from fire or flame.

When using this product

keep out of eyes, In case of contact with eyes, rinse thoroughly with water. Do not use on broken or irritated skin.

Stop use and ask a doctor if

irritation or redness develop and last more than 72 hours.

Keep out of reach of children.

If swallowed, get medical help or contact a Poison Control Center right away.

Directions

- Apply enough product to wet hands. Rub hands together until dry. Supervise children in use of this product.

Other information

- Do not store above 105 °F (40 °C).
- May discolor certain wood surfaces.

Inactive Ingredients:

Purified water, carbomer, triethanolamine, glycerin.